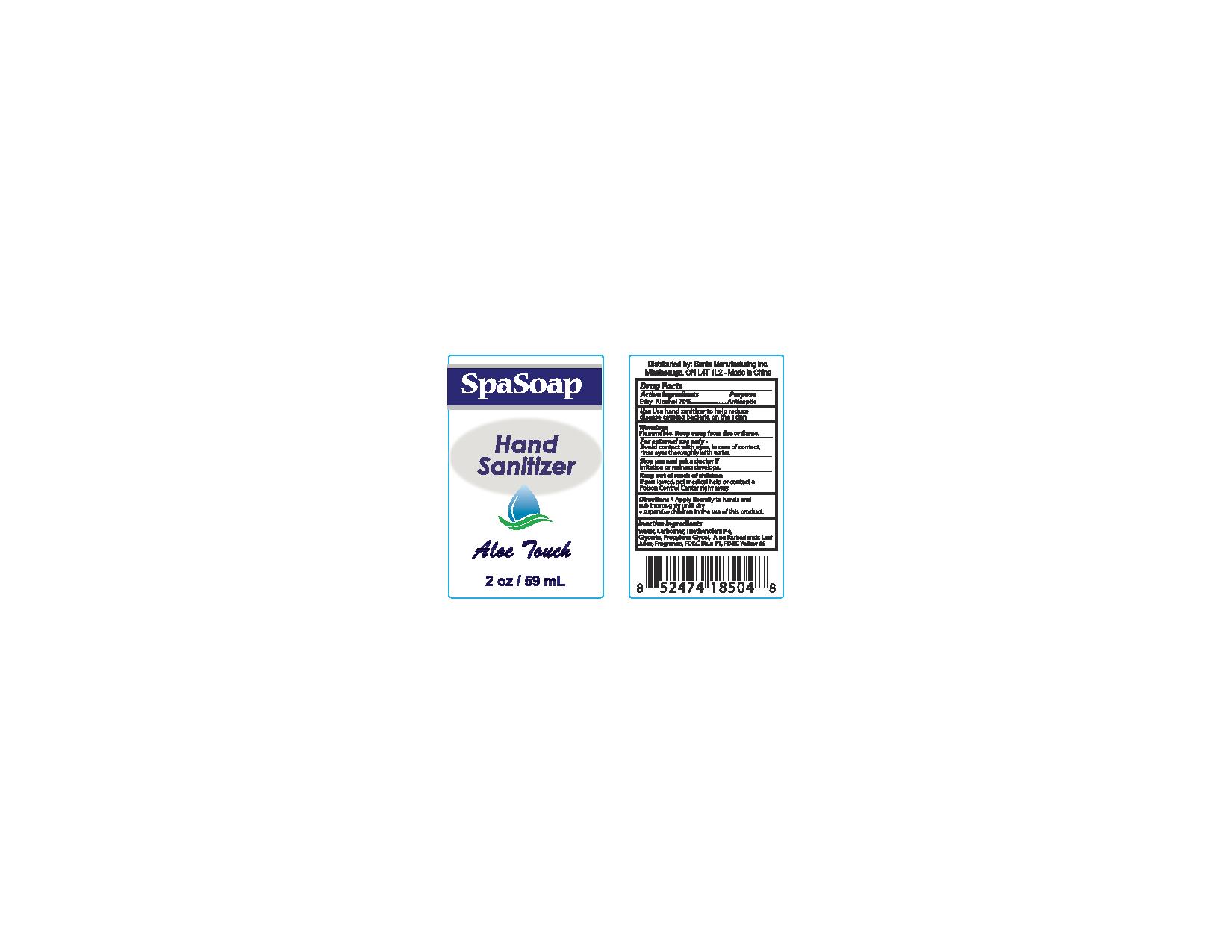 DRUG LABEL: Aloe Touch
NDC: 71020-010 | Form: LIQUID
Manufacturer: Sante Manufacturing Inc
Category: otc | Type: HUMAN OTC DRUG LABEL
Date: 20170310

ACTIVE INGREDIENTS: ALCOHOL 700 mL/1000 mL
INACTIVE INGREDIENTS: WATER; CARBOMER 940; GLYCERIN; ALOE VERA LEAF; FD&C BLUE NO. 1; FD&C YELLOW NO. 5

Active Ingredients - Ethyl Alcohol 70%

Purpose - Antiseptic

INDICATIONS AND USAGE

Use hand sanitizer to help reduce disease causing bacteria on the skin

Warnings

Flammable. Keep away from fire or flame

For external use only -

OTHER SAFETY INFORMATION

Avoid contact with eyes. In case of contact, rinse eyes thoroughly with water

Stop use and ask a doctor if irritation or redeness develops

Keep out of reach of children

If swallowed, get medical help or contact a POison Control Center right away

Directions

- Apply liberally to hands and rub thoroughly until dry
- supervise children in the use of this product

Inactive Ingredients

Water, Carbomer, Triethanolamine, Glycerin, Propylene Glycol, Aloe Barbadensis Leaf Juice, Fragrance, FD & C Blue# 1, FD & C Yellow# 5

PACKAGE LABEL

SpaSoap

Hand Sanitizer

Aloe Touch

2oz / 59ml